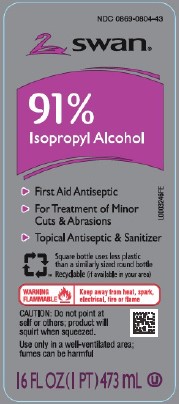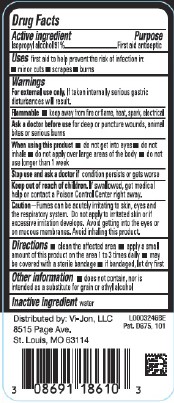 DRUG LABEL: Isopropyl Alcohol
NDC: 0869-0804 | Form: LIQUID
Manufacturer: Vi-Jon, LLC
Category: otc | Type: HUMAN OTC DRUG LABEL
Date: 20250616

ACTIVE INGREDIENTS: ISOPROPYL ALCOHOL 91 mL/100 mL
INACTIVE INGREDIENTS: WATER

Swan 804.003/804AA
91% Isopropyl Alcohol

Active ingredient

Isopropyl alcohol 91%

Purpose

First Aid Antiseptic

Uses

first aid to help provide the risk of infection in:

- minor cuts
- scrapes
- burns

Warnings

For external use only.If taken internally serious gastric disturbances will result.

Flammable

- keep away from fire or flame, heat, spark, electrical

Ask a doctor before use

for deep or punture wounds, animal bites or serious burns

When using this product

- do not get into eyes
- do not inhale
- do not apply over large areas of the body
- do not use longer than 1 week

Stop use and ask a doctor if

condition persists or gets worse

Keep out of reach of children.

If swallowed, get medical help or contact a Poison Control Center right away.

Caution

Fumes can be acutely irritating to skin, eyes and the respiratory system. Do not apply to irritated skn or if excessive irritation develops. Avoid getting into the eyes or on mucous membranes. Avoid inhaling this product.

Directions

- clean the affected area
- apply a small amount of this product on the area 1 to 3 times daily
- may be covered with sterile bandage
- if bandaged, let dry first

Other information

- does not contain, nor is intended as a substituted for grain or ethyl alcohol

Inactive ingredient

water

Adverse reaction

Distributed by: Vi-Jon, LLC

8515 Page Ave.

St. Louis, MO 63114

Pat. D675, 101

Principal display panel

NDC 0869-0804-43

SWAN®

91% Isoporpyl Alcohol

- First Aid Antiseptic
- For Treatment of Minor Cuts & Abrasions
- Topical Antiseptic & Santizier

Square bottle uses less plastic than a similarly sized round bottle.

Recyclable (if available in your area)

WARNING FLAMMALBE - Keep away from heat, spark electical, fire or flame

CAUTION: Do not point at self or other; product will squirt when squeezed

Use only in a well-ventilated area; fumes can be harmful

16 FL OZ (1 PT) 473 mL